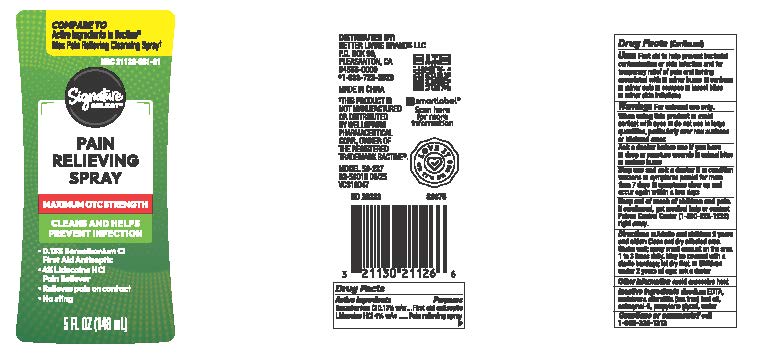 DRUG LABEL: Signature Select Pain Relieving
NDC: 21130-931 | Form: SPRAY
Manufacturer: Safeway/Albartsons
Category: otc | Type: HUMAN OTC DRUG LABEL
Date: 20251016

ACTIVE INGREDIENTS: BENZALKONIUM CHLORIDE 0.13 g/100 mL; LIDOCAINE HYDROCHLORIDE 4 g/100 mL
INACTIVE INGREDIENTS: WATER; EDETATE DISODIUM ANHYDROUS; OCTOXYNOL 9; MELALEUCA ALTERNIFOLIA (TEA TREE) LEAF OIL

Signature Select Pain Relieving Spray 5 oz

Active ingredients

Benzalkonium Cl 0.13%

LidocaineHCI 4%

Purpose

First aid antiseptic
Pain relieving

Uses

First aid to help prevent bacterial contamination or skin infection and for temporary relief of pain and itching associated with

■ minor burns

■ sunburn

■ minor cuts

■scrapes

■ insect bites

■ minor skin irritations

Warnings

For external use only

When using this product

■ avoid contact w th eyes

■ do not use in large quantities, particularly over raw surfaces or blistered areas

Ask a doctor before use if you have

■deep or puncture wounds

■ animalbites

■ serious burns

Stop use and ask a doctor if

■ condition worsens

■ symptoms persist for more than 7 days

■symptoms clear up and occur again w thin a few days

Keep out of reach of children and pets.

If swallowed, get medical help or contact Poison Control Center (1-800-222-1222) right away.

Directions

■Adults and children 2 years and older: Cleananddry affectedarea. Shake well;spray small amount on the area 1 to 3 times daily.
May be covered witha sterilebandage;let dry first.

■ Children under 2 years af age: ask a doctor

Other information

Avoid excessive heat

Inactive Ingredients

disodium EDTA, melaleuca alterniflia (tea Tree) leaf oil, octoxynol-9, propylene glycol, water

Questions or comments?

Call 1-866-1313